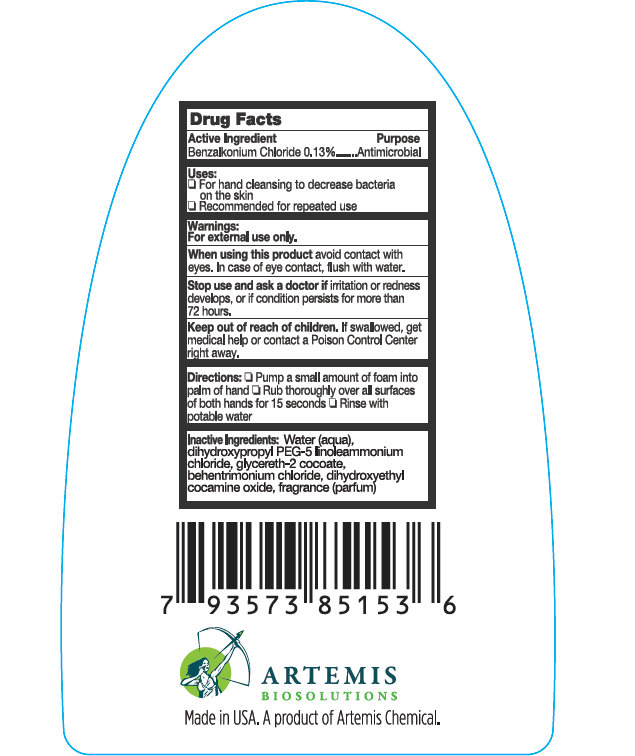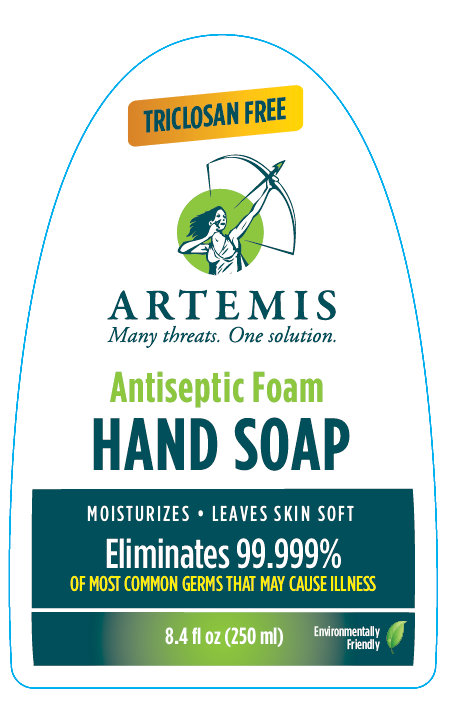 DRUG LABEL: ARTEMIS Alcohol-Free Antiseptic Foam Hand
NDC: 49765-410 | Form: SOAP
Manufacturer: Artemis Bio-Solutions Inc
Category: otc | Type: HUMAN OTC DRUG LABEL
Date: 20181219

ACTIVE INGREDIENTS: BENZALKONIUM CHLORIDE 1.3 mg/1 mL
INACTIVE INGREDIENTS: WATER; DIHYDROXYPROPYL PEG-5 LINOLEAMMONIUM CHLORIDE; GLYCERETH-2 COCOATE; BEHENTRIMONIUM CHLORIDE; DIHYDROXYETHYL COCAMINE OXIDE

ARTEMIS ALCOHOL-FREE Antiseptic Foam Hand Soap

Drug Facts

Active Ingredients

Benzalkonium Chloride 0.13%

Purpose

Antimicrobial

Uses

- For washing hands to decrease bacteria on the skin.
- Recommended for repeated use.

Warnings

- For external use only.

- Do not use in eyes. If contact occurs, flush eyes with water.

- Stop use and ask a doctor if irritation or redness develops. If condition persists for more than 72 hours, consult a doctor.

- Keep out of reach of children. If swallowed, get medical help or contact a Poison Control Center right away.

Directions

- Pump a small amount of foam into palm of hand.
- Rub thoroughly over all surfaces of both hands for 15 seconds.
- Rinse with potable water.

Inactive Ingredients

Water, dihydroxypropyl PEG-5 linoleammonium chloride, glycereth-2cocoate, behentrimonium chloride, dihydroxyethyl cocamine oxide, fragrance

ARTEMIS BIOSOLUTIONS

Manufactured by Artemis BioSolutions.

960 N. Industrial Dr., Ste.4 Elmhurst, IL 60126.

Made in USA.

PACKAGE LABEL

TRICLOSAN FREE
ARTEMIS
Many threats. One solution
ANTISEPTIC FOAM HAND SOAP
MOISTURIZES
LEAVES SKIN SOFT
Eliminates 99.999%
OF MOST COMMON GERMS THAT MAY CAUSE ILLNESS
Environmentally Friendly
8.4 floz (250ml)